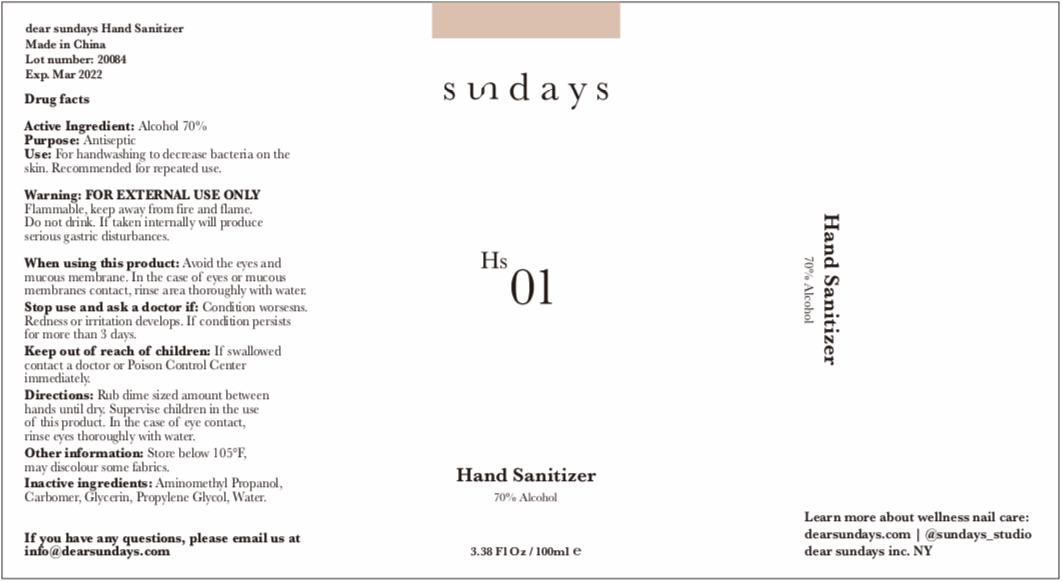 DRUG LABEL: Hand Sanitizer
NDC: 77366-002 | Form: GEL
Manufacturer: NTML Group Ltd
Category: otc | Type: HUMAN OTC DRUG LABEL
Date: 20200505

ACTIVE INGREDIENTS: ALCOHOL 70 mL/100 mL
INACTIVE INGREDIENTS: WATER; PROPYLENE GLYCOL; CARBOMER HOMOPOLYMER, UNSPECIFIED TYPE; GLYCERIN; AMINOMETHYLPROPANOL

Dear Sundays 70% Alcohol Hand Sanitizer (3.38 Fl Oz / 100ml)

Hand Sanitizer with NDC 00000-000 is a a human over the counter drug product labeled by NTML Group Ltd. The generic name of Hand Sanitizer is alcohol. The product's dosage form is gel and is administered via topical form.

Active Ingredient(s)

Alcohol 70% v/v. Purpose: Antiseptic

Purpose

Antiseptic, Hand Sanitizer

Use

For handwashing to decrease bacteria on the skin

Recommended for repeated use

Warnings

For external use only

Flammable, keep away from fire and flame

Do not drink

If taken internally will produce serious gastric disturbances

Do not use

- in children less than 2 months of age
- on open skin wounds

When using this product avoid the eyes and mucous membrane

In the case of eyes or mucous membranes contact, rinse area thoroughly with water

Stop use and ask a doctor if condition worsens, redness or irritation develops

If condition persists for more than 3 days

Keep out of reach of children. If swallowed contact a doctor or Poison Control Center immediately.

Directions

Rub dime sized amount between hands until dry

Supervise children in the use of this product

In the case of eye contact, rinse eyes thoroughly with water

Other information

Store below 105 F

May discolour some fabrics

Inactive ingredients

Aminomethyl Propanol, Carbomer, Glycerin, Propylene Glycol, Water.

Package Label - Principal Display Panel

70% Alcohol Gel

1000 mL (3.38 fl oz)